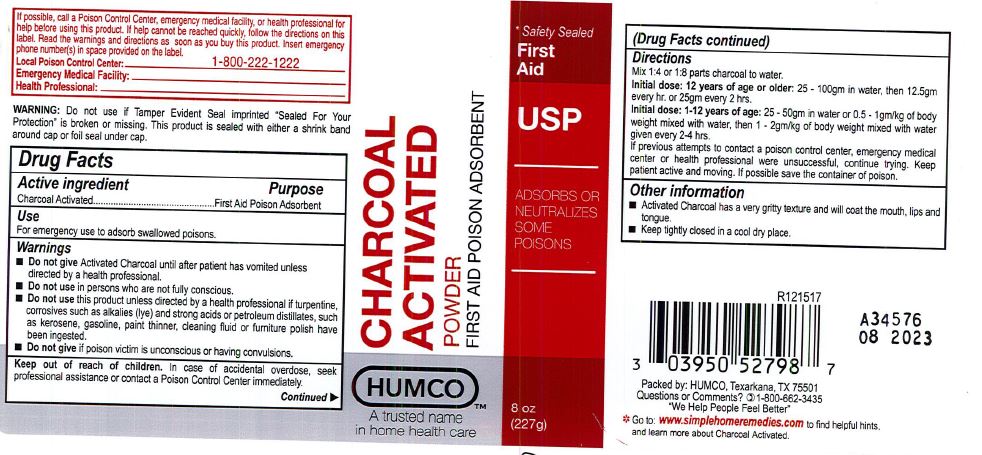 DRUG LABEL: Humco Charcoal Activated
NDC: 0395-0527 | Form: POWDER
Manufacturer: Humco Holding Group. Inc.
Category: otc | Type: HUMAN OTC DRUG LABEL
Date: 20231215

ACTIVE INGREDIENTS: ACTIVATED CHARCOAL 1000 mg/1 g
INACTIVE INGREDIENTS: WATER

Humco Charcoal Activated

Drug Facts

Active Ingredient

Charcoal Activated

Purpose

First Aid Poison Adsorbent

OTHER SAFETY INFORMATION

If possibl;e, call a Poison Control Center, emergency facility, or health professional for help before using this product. If help cannot be reached quickly, follow the directions in this label. Read the warnings and directions as soon as you buy this product. Insert emergency phone number(s) in space proviedd on the label.

Poison Control Center: 1-800-222-1222

Emergency Medical Facility: ____________________

Health Professional: _____________________

Warning:

Do not use if Tamper Evident Seal imprinted "Sealed for Your Protection" is broken or missing. This product is sealed with either a shrink band around the cap or foil seal under cap.

Use

For emergency use to adsorb swallowed poisons.

Warnings

- Do not give Activated Charcoal until after patient has vomited unless directed by a health professional.
- Do not use in persons who are not fully conscious.
- Do not use this product unless directed by a health professional if turpentine, corrosives such as alkalies (lye) and strong acids or petroleum didtillates, such as kerosene, gasoline, paint thinner, cleaning fluid or furniture polish have been ingested.
- Do not give if poison victim is unconscious or having convulsions. Keep patient active and moving.

Keep out of reach of children.

In case of accidental overdose, seek professional assistance or contact a Poison Control Center immediately.

Directions for 1 oz bottle

When Activated Charcoal is indicated for use, give 3 to 4 heaping tablespoonfulls (20 to 30 g) mixed in a minimum of 8 ounces of liquid or as directed by a health professional. If an emergency, fill this bottle with water.

Mix well and have poison victim drink all of this mixture. Repeat dose immediately, if possible. If previous attempts to contact a poison control center, emergency medical center or health professional were unsuccessful, continue trying. If possible save the container of poison.

Directions for 8 oz bottle

When Activated Charcoal is indicated, the usual dose is as follows:

- 0-10 years of age: 1 to 3 heaping tablespoonfulls (10 -25 g) mixed in a minimum of 8 ounces of liquid.
- 10 - 12 yrs of age: 3 - 6 tablespoonfulls (25 - 50 g) mixed in a minimum of 8 ounces of liquid.
- Greater than 12 years of age: 3 to 12 tablespoonfulls (25 - 100g) mixed with a minimum of 8 ounces of liquid or as directed by a health professional. mix well and have poison victim drink all of this mixture. Repeat dose immediately, if possible. If the previous attempts to contact poison control center, emergency medical center or health professional were unsuccessful, continue trying. If possible save the container of poison.

Other Information

- Activated Charcoal has a very gritty texture and will coat the mouth, lips and tonge.
- Keep tightly closed in a cool dry place.

Inactive Ingredients

None